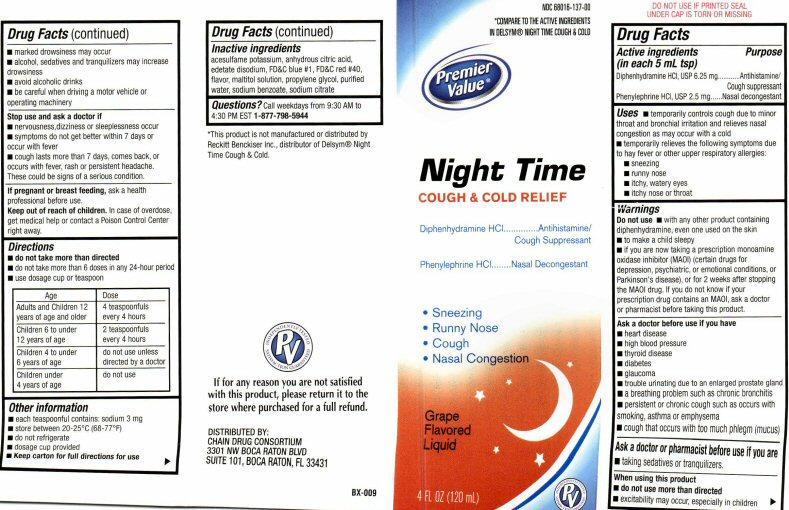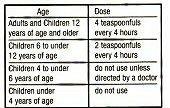 DRUG LABEL: Night Time Cough and Cold Relief
NDC: 68016-137 | Form: LIQUID
Manufacturer: Chain Drug Consortium, LLC
Category: otc | Type: HUMAN OTC DRUG LABEL
Date: 20130401

ACTIVE INGREDIENTS: DIPHENHYDRAMINE HYDROCHLORIDE 6.25 mg/5 mL; PHENYLEPHRINE HYDROCHLORIDE 2.5 mg/5 mL
INACTIVE INGREDIENTS: ACESULFAME POTASSIUM; ANHYDROUS CITRIC ACID; EDETATE DISODIUM; FD&C BLUE NO. 1; FD&C RED NO. 40; MALTITOL; PROPYLENE GLYCOL; WATER; SODIUM BENZOATE; SODIUM CITRATE

Active ingredients

Drug Facts

Active ingredients
(in each 5 mL tsp)

Diphenhydramine HCL, USP 6.25 mg

Phenylephrine HCL, USP 2.5.mg

Purpose

Antihistamine / Cough suppressant

Nasal decongestant

Keep out of reach of children

In case of overdose, get medical help or contact a Poison Control center right away.

Uses

- temporarily controls cough due to minor throat and bronchial irritation and relieves nasal congestion as may occur with a cold
- temporarily relieves the following symptoms due to hay fever or other upper respiratory allergies:
-
  - sneezing
  - runny nose
  - itchy, watery eyes
  - itchy nose or throat

Warnings

Do not use

- with any other product containing diphenhydramine, even one used on the skin
- to make a child sleepy
- if you are now taking a prescription monoamine oxidase inhibitor (MAOI) (certain drugs for depression, psychiatric or emotional conditions, or Parkinson’s disease), or for two weeks after stopping the MAOI drug. If you do not know if your prescription drug contains an MAOI, ask a doctor or a pharmacist before taking this product.

Ask a doctor before use if you have

- heart disease
- high blood pressure
- thyroid disease
- diabetes
- glaucoma
- trouble urinating due to an enlarged prostate gland
- a breathing problem such as chronic bronchitis
- persistent or chronic cough such as occurs with smoking, asthma or emphysema
- cough that occurs with too much phlegm (mucus)

Ask a doctor or pharmacist before use if you are

- taking sedatives or tranquilizers.

When using this product

- do not use more than directed
- excitability may occur, especially in children
- marked drowsiness may occur
- alcohol, sedatives and tranquilizers may increase drowsiness
- avoid alcohol drinks
- be careful when driving a motor vehicle or operating machinery

Stop use and ask a doctor if

- nervousness, dizziness or sleeplessness occur
- symptoms do not get better within 7 days or occur with fever
- cough lasts more than 7 days, comes back, or occurs with fever, rash or persistent headache
- These could be signs of a serious condition.

If pregnant or breast feeding,

ask a health professional before use.

Directions

- do not take more than directed
- do not take more than 6 doses in any 24-hour period
- use dose cup or teaspoon

Other information

- each tablespoonful contains: sodium 3 mg
- store between 20-25° C (68-77° F)
- do not refrigerate
- dosage cup provided
- Keep carton for full directions for use

Inactive ingredients

acesulfame potassium, anhydrous citric acid, edetate disodium, FD and C Blue # 1, FD and C Red # 40, flavor, maltitol solution, propylene glycol, purified water, sodium benzoate, sodium citrate

Questions?

Call weekdays from 9:30 AM to 4:30 PM EST 1-877-798-5944

Product Label

NDC68016-137-00
*COMPARE TO THE ACTIVE INGREDIENTS IN DELSYM® NIGHT TIME COUGH and COLD
Premier Value®
NIGHT TIME
COUGH and COLD RELIEF
Diphenhydramine HCL .......................Antihistamine/Cough Suppressant
Phenylephrine HCL ...........................Nasal Decongestant

- Sneezing
- Runny Nose
- Cough
- Nasal Congestion

Grape Flavored Liquid
4 FL OZ (120 mL)

INDEPENDENTLY TESTED SATISFACTION GUARANTEED PV
DO NOT USE IF PRINTED SEAL UNDER CAP IS TORN OR MISSING
*This product is not manufactured or distributed by Reckitt Benckiser Inc. distributor of Children’s Mucinex® Multisymptom Cold
If for Any reason you are not satisfied with this product, please return it to the store where purchased for a full refund.

DISTRIBUTED BY
CHAIN DRUG CONSORTIUM
3301 NW BOCA RATON BLVD
SUITE 101, BOCA RATON, FL 33431
BX-009